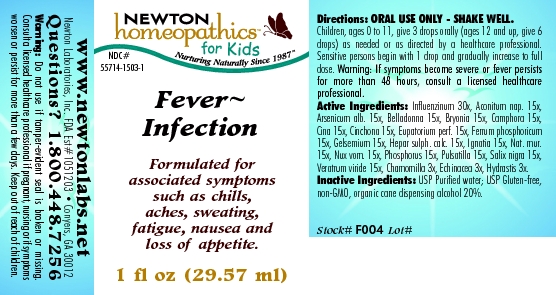 DRUG LABEL: Fever Infection 
NDC: 55714-1503 | Form: LIQUID
Manufacturer: Newton Laboratories, Inc.
Category: homeopathic | Type: HUMAN OTC DRUG LABEL
Date: 20110301

ACTIVE INGREDIENTS: Influenza A Virus 30 [hp_X]/1 mL; Aconitum Napellus 15 [hp_X]/1 mL; Arsenic Trioxide 15 [hp_X]/1 mL; Atropa Belladonna 15 [hp_X]/1 mL; Bryonia Alba Root 15 [hp_X]/1 mL; Camphor (natural) 15 [hp_X]/1 mL; Artemisia Cina Pre-flowering Top 15 [hp_X]/1 mL; Cinchona Officinalis Bark 15 [hp_X]/1 mL; Eupatorium Perfoliatum Flowering Top 15 [hp_X]/1 mL; Gelsemium Sempervirens Root 15 [hp_X]/1 mL; Calcium Sulfide 15 [hp_X]/1 mL; Strychnos Ignatii Seed 15 [hp_X]/1 mL; Sodium Chloride 15 [hp_X]/1 mL; Strychnos Nux-vomica Seed 15 [hp_X]/1 mL; Phosphorus 15 [hp_X]/1 mL; Pulsatilla Vulgaris 15 [hp_X]/1 mL; Salix Nigra Bark 15 [hp_X]/1 mL; Veratrum Viride Root 15 [hp_X]/1 mL; Matricaria Recutita 3 [hp_X]/1 mL; Echinacea, Unspecified 3 [hp_X]/1 mL; Goldenseal 3 [hp_X]/1 mL; Ferrosoferric Phosphate 15 [hp_X]/1 mL; Influenza B Virus 30 [hp_X]/1 mL
INACTIVE INGREDIENTS: Alcohol

Fever - Infection

INDICATIONS & USAGE SECTION

Fever - Infection Formulated for associated symptoms such as chills, aches, sweating, fatigue, nausea and loss of appetite.

DOSAGE & ADMINISTRATION SECTION

Directions: ORAL USE ONLY - SHAKE WELL. Children, ages 0 to 11, give 3 drops orally (ages 12 and up, give 6 drops) as needed or as directed by a healthcare professional. Sensitive persons begin with 1 drop and gradually increase to full dose. Warning: If symptoms become severe or fever persists for more than 48 hours, consult a licensed health care professional.

OTC - ACTIVE INGREDIENT SECTION

Influenzinum 30x, Aconitum nap. 15x, Arsenicum alb. 15x, Belladonna 15x, Bryonia 15x, Camphora 15x, Cina 15x, Cinchona 15x, Eupatorium perf. 15x, Ferrum phosphoricum 15x, Gelsemium 15x, Hepar sulph. calc. 15x, Ignatia 15x, Nat. mur.15x, Nux vom. 15x, Phosphorus 15x, Pulsatilla 15x, Salix nigra 15x, Veratrum viride 15x, Chamomilla 3x, Echinacea 3x, Hydrastis 3x.

OTC - PURPOSE SECTION

Formulated for associated symptoms such as chills, aches, sweating, fatigue, nausea and loss of appetite.

INACTIVE INGREDIENT SECTION

Inactive Ingredients: USP Purified Water; USP Gluten-free, non-GMO, organic cane dispensing alcohol 20%.

QUESTIONS SECTION

www.newtonlabs.net Newton Laboratories, Inc. FDA Est # 1051203 - Conyers, GA 30012
Questions? 1.800.448.7256

WARNINGS SECTION

Warning: Do not use if tamper - evident seal is broken or missing. Consult a licensed healthcare professional if p. regnant, nursing or if symptoms worsen or persist for more than a few days. Keep out of reach of children.

OTC - PREGNANCY OR BREAST FEEDING SECTION

Consult a licensed healthcare professional if pregnant, nursing or if symptoms worsen or persist for more than a few days.

OTC - KEEP OUT OF REACH OF CHILDREN SECTION

Keep out of reach of children.